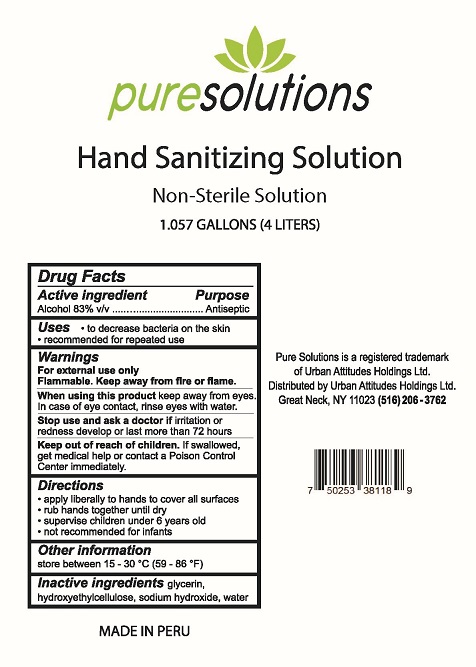 DRUG LABEL: Pure Solutions Hand Sanitizing
NDC: 77185-002 | Form: SOLUTION
Manufacturer: Urban Attitudes Holdings Ltd
Category: otc | Type: HUMAN OTC DRUG LABEL
Date: 20200512

ACTIVE INGREDIENTS: ALCOHOL 83 L/100 L
INACTIVE INGREDIENTS: SODIUM HYDROXIDE; HYDROXYETHYL CELLULOSE, UNSPECIFIED; WATER; GLYCERIN

Pure Solutions Hand Sanitizer

Drug Facts

Active ingredient

Alcohol 83% v/v

Purpose
Antiseptic

Uses

- to decrease bacteria on the skin
- recommended for repeated use

Warnings
For external use only.
Flammable. Keep away from heat or flame.

When using this product keep away from eyes. In case of eye contact, rinse eyes with water.

Stop use and ask a doctor if irritation or redness develop or last more than 72 hours.

Keep out of reach of children. If swallowed, get medical help or contact a Poison Control Center immediately.

Directions

- apply liberally to hands to cover all surfaces
- rub hands together until dry
- supervise children under 6 years old
- not recommended for infants

Other information

store between 15-30°C (59-86°F)

Inactive ingredients

glycerin, hydroxyethylcellulose, sodium hydroxide, water

Pure Solutions is a registered trademark of Urban Attitudes Holdings Ltd.

Distributed by:

Urban Attititudes Holdings Ltd.

Great Neck, NY 11023

(516) 206-3672

MADE IN PERU

PACKAGE LABEL

puresolutions

Hand Sanitizing Solution

Non-Sterile Solution

1.057 GALLONS (4 LITERS)